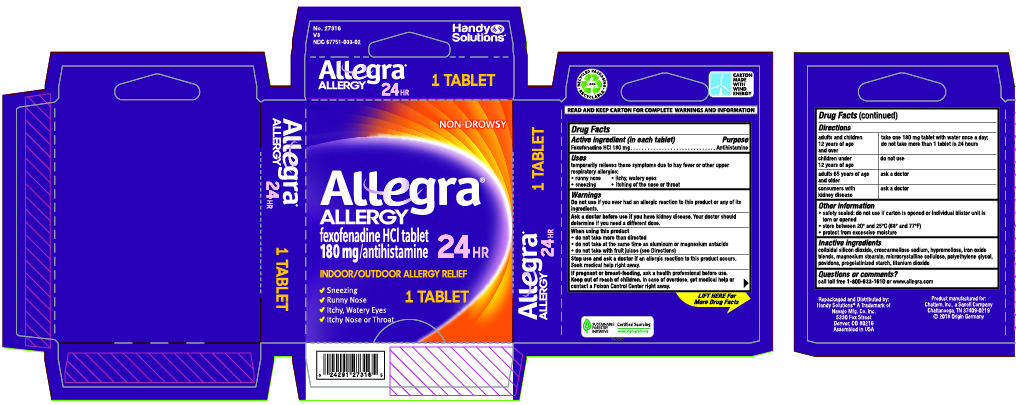 DRUG LABEL: Allegra Allergy
NDC: 67751-033 | Form: TABLET, FILM COATED
Manufacturer: Navajo Manufacturing Company Inc.
Category: otc | Type: HUMAN OTC DRUG LABEL
Date: 20241002

ACTIVE INGREDIENTS: FEXOFENADINE HYDROCHLORIDE 180 mg/1 1
INACTIVE INGREDIENTS: SILICON DIOXIDE; CROSCARMELLOSE SODIUM; HYPROMELLOSES; MAGNESIUM STEARATE; CELLULOSE, MICROCRYSTALLINE; POLYETHYLENE GLYCOL, UNSPECIFIED; POVIDONE; TITANIUM DIOXIDE

Allegra Allergy

Active ingredient (in each tablet)

Fexofenadine HCl 180 mg

Purpose

Antihistamine

Uses

temporarily relieves these symptoms due to hay fever or upper respiratory allergies:

- runny nose
- sneezing
- itchy, watery eyes
- itching of the nose or throat

Warnings

Do not use

if you have ever had an allergic reaction to this product or any of its ingredients.

Ask a doctor before use if you have

kidney desease. Your doctor should determine ifyou need a different dose.

When using this product

- do not take more than directed
- do not take at the same time as aluminum or magnesium antacids
- do not take with fruit juices (see Directions)

Stop use and ask a doctor if

an allergic reaction to this product occurs. Seek medical help right away.

If pregnant or breast-feeding,

ask a health professional before use.

Keep out of reach of children.

In case of overdose, get medical help or contact a Poison Control Center right away.

Directions

adults and children 12 years of age and over | take one 180mg tablet with water once a day; do not take more than 1 tablet in 24 hours
children under 12 years of age | do not use
adults 65 years of age and older | ask a doctor
consumers with kidney disease | ask a doctor

Other information

- safety sealed: do not use if individual blister is open or torn
- store between 20o and 25o C (68o and 77oF)
- protect from excessive moisture

Inactive ingredients

colloidal silicone dioxide, croscarmellose sodium, hypromellose, iron oxide blends, magnesium stearate, microcrystalline cellulose, polyethylene glycol, povidone, pregelatinized starch, titanium dioxide

Questions or comments?

Call toll-free 1-800-633-1610 or www.allegra.com